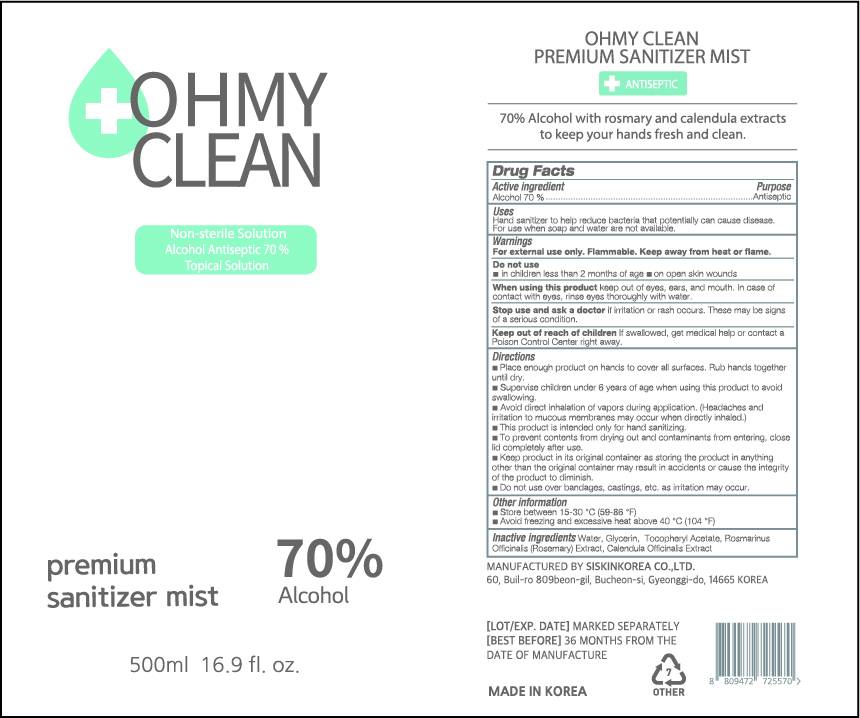 DRUG LABEL: OH MY CLEAN PREMIUM SANITIZER MIST
NDC: 74514-9570 | Form: LIQUID
Manufacturer: SISKINKOREA CO.,LTD.
Category: otc | Type: HUMAN OTC DRUG LABEL
Date: 20200403

ACTIVE INGREDIENTS: ALCOHOL 350 mL/500 mL
INACTIVE INGREDIENTS: GLYCERIN; .ALPHA.-TOCOPHEROL ACETATE; CALENDULA OFFICINALIS WHOLE; WATER; ROSEMARY

500ml_70%_gel_OH MY CLEAN PREMIUM SANITIZER MIST [74514-9570-1]